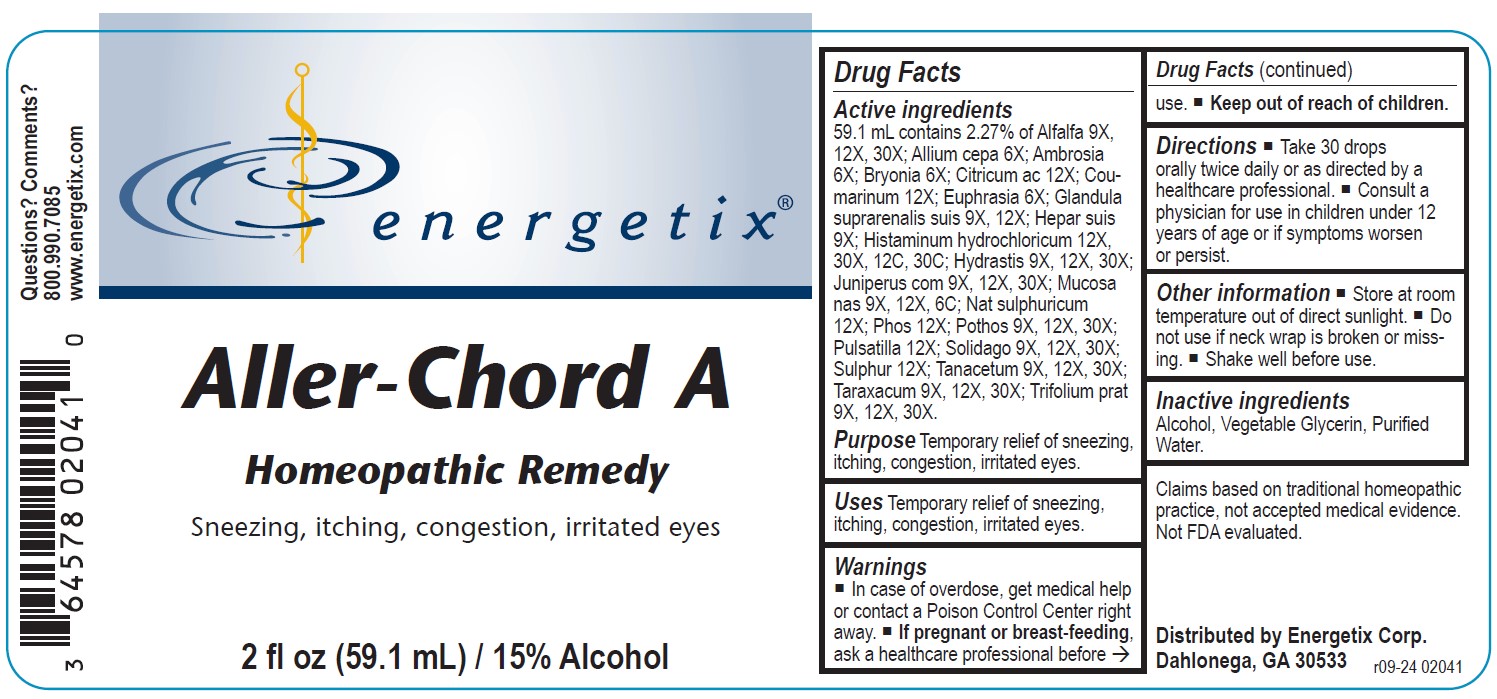 DRUG LABEL: Aller-Chord A
NDC: 64578-0057 | Form: LIQUID
Manufacturer: Energetix Corporation
Category: homeopathic | Type: HUMAN OTC DRUG LABEL
Date: 20241211

ACTIVE INGREDIENTS: PULSATILLA VULGARIS 12 [hp_X]/1 mL; SOLIDAGO VIRGAUREA FLOWERING TOP 9 [hp_X]/1 mL; SULFUR 12 [hp_X]/1 mL; TANACETUM VULGARE TOP 9 [hp_X]/1 mL; TARAXACUM OFFICINALE 9 [hp_X]/1 mL; TRIFOLIUM PRATENSE FLOWER 9 [hp_X]/1 mL; ALFALFA 9 [hp_X]/1 mL; ONION 6 [hp_X]/1 mL; AMBROSIA ARTEMISIIFOLIA 6 [hp_X]/1 mL; BRYONIA ALBA ROOT 6 [hp_X]/1 mL; ANHYDROUS CITRIC ACID 12 [hp_X]/1 mL; COUMARIN 12 [hp_X]/1 mL; EUPHRASIA STRICTA 6 [hp_X]/1 mL; SUS SCROFA ADRENAL GLAND 9 [hp_X]/1 mL; PORK LIVER 9 [hp_X]/1 mL; HISTAMINE DIHYDROCHLORIDE 12 [hp_X]/1 mL; GOLDENSEAL 9 [hp_X]/1 mL; JUNIPER BERRY 9 [hp_X]/1 mL; SUS SCROFA NASAL MUCOSA 9 [hp_X]/1 mL; SODIUM SULFATE 12 [hp_X]/1 mL; PHOSPHORUS 12 [hp_X]/1 mL; SYMPLOCARPUS FOETIDUS ROOT 9 [hp_X]/1 mL
INACTIVE INGREDIENTS: WATER; ALCOHOL; GLYCERIN

Aller-Chord A

ACTIVE INGREDIENT

Active ingredients 59.1 mL contains 2.27% of: Alfalfa 9X, 12X, 30X; Allium cepa 6X; Ambrosia 6X; Bryonia 6X, Citricum ac 12X; Coumarinum 12X, Euphrasia 6X; Glandula suprarenalis suis 9X, 12X; Hepar suis 9X, Histaminum hydrochloricum 12X, 30x, 12C, 30C; Hydrastis 9X, 12X, 30X; Juniperus com 9X, 12X, 30X; Mucosa nas 9X, 12X, 6C; Nat sulphuricum 12X; Phos 12X; Pothos 9X, 12X, 30X, Pulsatilla 12X; Solidago 9X, 12X, 30X, Sulphur 12X; Tanacetum 9X, 12X, 30X; Trifolium prat 9X, 12X, 30X.

Claims based on traditional homeopathic practice, not accepted medical evidence. Not FDA evaluated.

INDICATIONS AND USAGE

UsesTemporary relief of sneezing, itching, congestion, irritated eyes.

WARNINGS

In case of overdose, get medical help or call a Poison Control Center right away.
If pregnant or breast-feeding,ask a health professional before use.

Keep out of reach of children.

DOSAGE AND ADMINISTRATION

Take 30 drops orally twice daily or as directed by a healthcare professional.
Consult a physician for use in children under 12 years of age or if symptoms worsen or persist.

Other information

- Store at room temperature out of direct sunlight.
- Do not use if neck wrap is broken or missing.
- Shake well before use.

Inactive ingredients Alcohol, Vegetable Glycerin, Purified Water

QUESTIONS

Distributed by
Energetix Corp
Dahlonega, GA 30533

Questions? 800.990.7085

www.energetix.com

PACKAGE LABEL

energetix

Aller-Chord A

Homeopathic Remedy

Sneezing, itching, congestion, irritated eyes

2 fl oz (59.1 mL) / 15% Alcohol

PURPOSE

Purpose Temporary relief of sneezing, itching, congestion, irritated eyes.